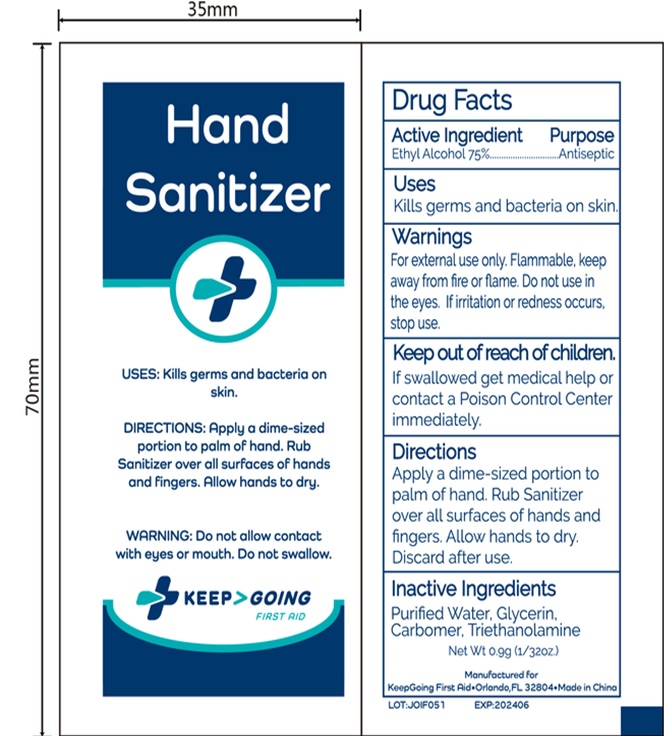 DRUG LABEL: Keep Going Hand Sanitizer
NDC: 71734-346 | Form: LIQUID
Manufacturer: JIANGMEN SHUIZIRUN SANITARY ARTICLES CO., LTD.
Category: otc | Type: HUMAN OTC DRUG LABEL
Date: 20210708

ACTIVE INGREDIENTS: ALCOHOL 75 g/100 g
INACTIVE INGREDIENTS: GLYCERIN; WATER; TROLAMINE

Drug Fact

Active Ingredient

Ethyl Alcohol 75%

Purpose

Antiseptic

Uses

Kills germs and bacteria on skin.

Warnings

For external use only. Flammable, keep away from fire or flame.

Do not use in the eyes..

If irritation or redness occurs, stop use.

Keep out of reach of children.

If swallowed get medical help or contact a Posion Control Center immediately.

Directions

Apply a dime-sized portion to palm of hand. Rub Sanitizer over all surfaces of hands and fingers .Allow hands to dry. Discard after use.

Inactive Ingredients

Purified Water, Glycerin, Carbomer, Triethanolamine.